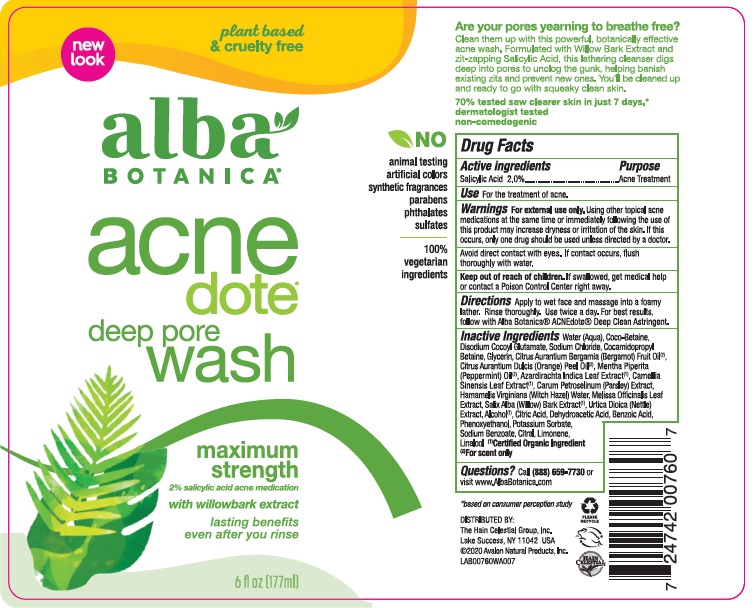 DRUG LABEL: AL0076001 Alba Botanica Acnedote Deep Pore Wash
NDC: 61995-2060 | Form: LOTION
Manufacturer: The Hain Celestial Group, Inc.
Category: otc | Type: HUMAN OTC DRUG LABEL
Date: 20240731

ACTIVE INGREDIENTS: SALICYLIC ACID 2 g/100 g
INACTIVE INGREDIENTS: ALCOHOL 95%; CITRAL; COCO-BETAINE; CITRIC ACID MONOHYDRATE; WATER; DISODIUM COCOYL GLUTAMATE; SODIUM CHLORIDE; COCAMIDOPROPYL BETAINE; GLYCERIN; HAMAMELIS VIRGINIANA TOP WATER; PHENOXYETHANOL; AZADIRACHTA INDICA LEAF; BERGAMOT OIL; PEPPERMINT OIL; POTASSIUM SORBATE; CAMELLIA SINENSIS WHOLE; TERT-BUTYLBENZOIC ACID (MIXED ISOMERS); WILLOW BARK; DEHYDROACETIC ACID; SODIUM BENZOATE; ORANGE PEEL; MELISSA OFFICINALIS LEAF; PARSLEY OIL; URTICA DIOICA LEAF; LIMONENE, (+)-; LINALOOL, (+)-

AL00760 Alba Botanica Acnedote Deep Pore Wash
Formula PF161797-02

ACTIVE INGREDIENTS

Salicylic Acid 2.0%

INDICATIONS AND USAGE

- For the treatment of acne

WARNINGS

For external use only. Using other topical acne medications at the same time or immediately following the use of this product may increase dryness or irritation of the skin. If this occurs,only one drug should be used unless directed by a doctor.

Avoid direct contact with eyes. If contact occurs, flush thoroughly with water.

Keep out of reach of children. If swallowed, get medical help or contact a Poison Control Center right away.

DOSAGE AND ADMINISTRATION

Apply to wet face and massage into a foamy lather. Rinse throughly. Use tvice a day.For best results follow with Alba Botanica Deep Clean Astrigen.

Keep out of reach of children. If swallowed, get medical help or contact a Poison Center right away.

INACTIVE INGREDIENT

Water (Aqua), Coco-Betaine, Disodium Cocoyl Glutamate, Sodium Chloride, Cocamidopropyl Betaine, Glycerin, Citrus Aurantium Bergamia (Bergamot) Fruit Oil, Citrus Aurantium Dulcis (Orange) Peel Oil, Mentha Piperita (Peppermint) Oil, Azadirachta Indica Leaf Extract (1), Camellia Sinensis Leaf Extract (1), Carum Petroselinum (Parsley) Extract, Hamamelis Virginiana (Witch Hazel) Water, Melissa Officinalis Leaf Extract, Salix Alba (Willow) Bark Extract (1), Urtica Dioica (Nettle) Extract, Alcohol (1), Citric Acid, Dehydroacetic Acid, Benzoic Acid, Phenoxyethanol, Potassium Sorbate, Sodium Benzoate, Citral, Limonene, Linalool

(1) Cerified Organic Ingredient

PURPOSE

Acne Treatment